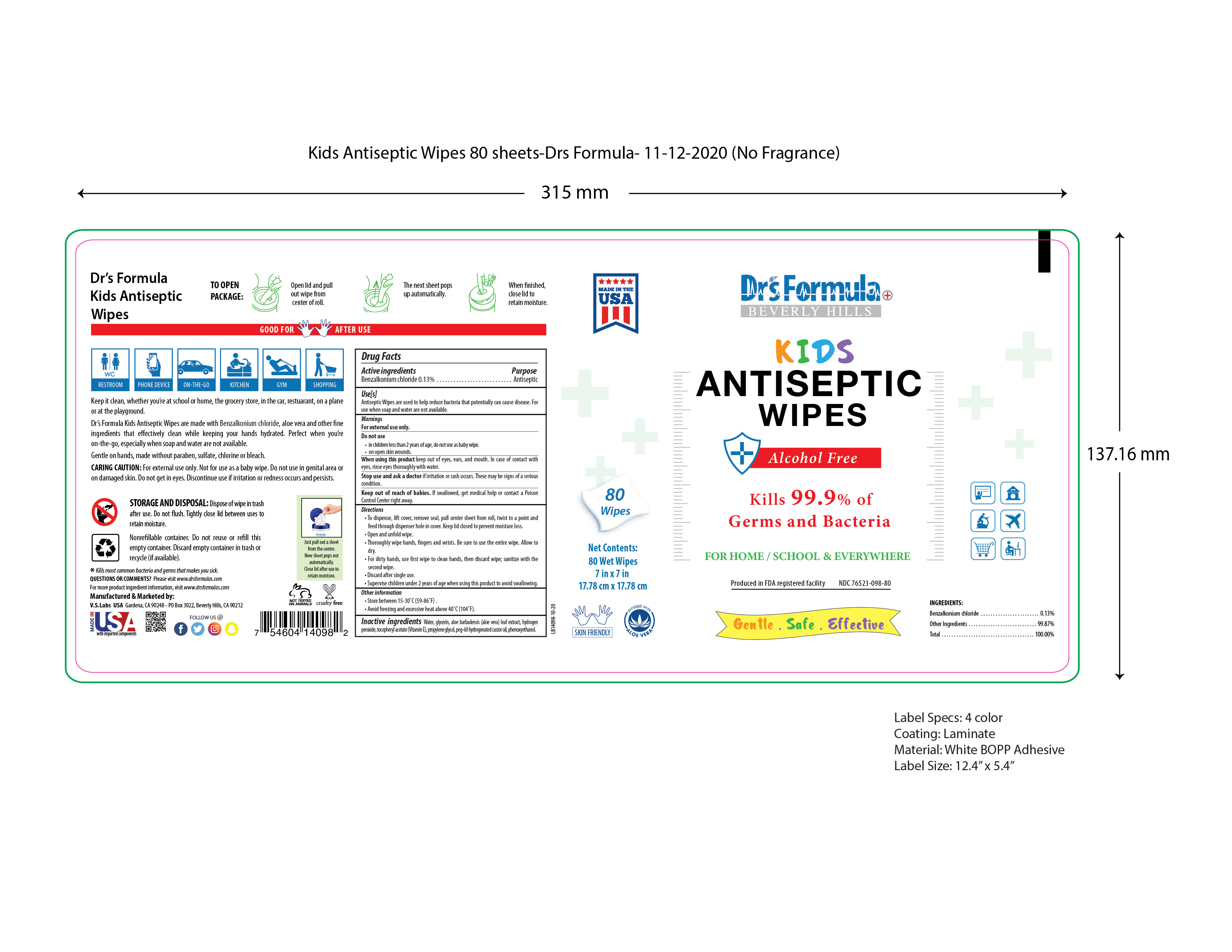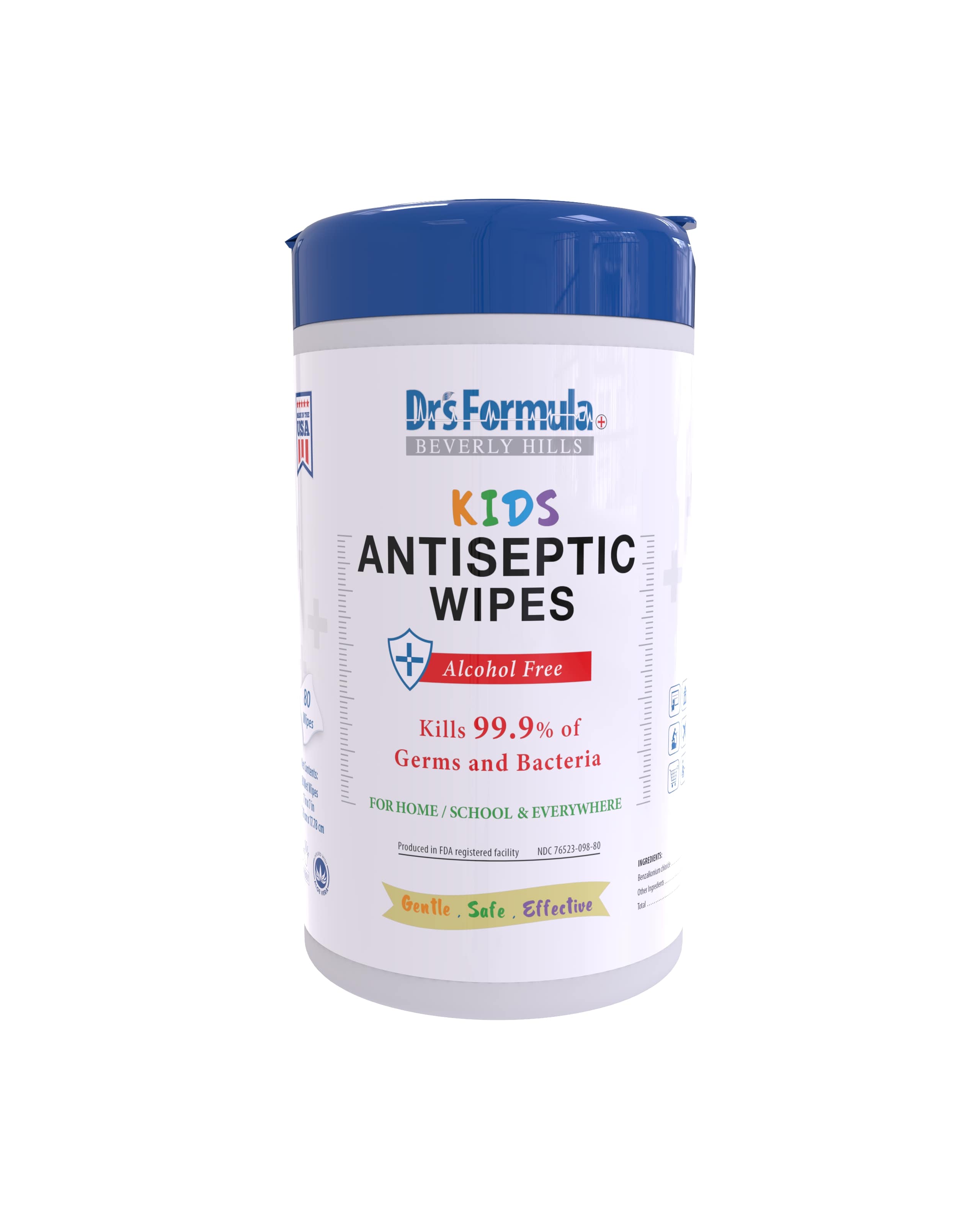 DRUG LABEL: KIDS Antiseptic Wipes
NDC: 76523-098 | Form: CLOTH
Manufacturer: Valley of the Sun Cosmetics LLC
Category: otc | Type: HUMAN OTC DRUG LABEL
Date: 20201113

ACTIVE INGREDIENTS: BENZALKONIUM CHLORIDE 0.13 g/100 g
INACTIVE INGREDIENTS: ALOE VERA LEAF 0.3 g/100 g; WATER 97.14 g/100 g; GLYCERIN 1.45 g/100 g; PROPYLENE GLYCOL 0.3 g/100 g; PHENOXYETHANOL 0.15 g/100 g; HYDROGEN PEROXIDE 0.125 g/100 g; ALPHA-TOCOPHEROL ACETATE 0.01 g/100 g; PEG-60 HYDROGENATED CASTOR OIL 0.4 g/100 g

Antiseptic Wipes

Active Ingredients

Benzalkonium Chloride 0.13%

Purpose

Antiseptic

Uses

Antiseptic Wipes are used to help reduce bacteria that potentiallyy can cause disease. For use when soap and water are not available.

Warnings

For external use only.

Do not use

- in children less than 2 years of age, do not use as baby wipe.
- on open skin wounds.

When using this product

Keep out of eyes, ears, and mouth. In case of contact with eyes, rinse eyes thoroughly with water.

Stop use and ask a doctor

If irritation or rash occurs. These may be signs of a serious condition.

Keep out of reach of babies

If swallowed, get medical help or contact a poison Control Center right away

Directions

- To dispense, lift cover, remove seal, pull center sheet from roll, twist to a point and feed through dispenser hole in cover. Keep lid closed to prevent moisture loss.
- Open and unfold wipe
- Thoroughly wipe hands, fingers, and wrists. Be sure to use the entire wipe. Allow to dry.
- For dirty hands, use first wipe to clean hands, then discard wipe; sanitize with the second wipe.
- Discard after single use
- Supervise children under 2 years of age when using this product to avoid swallowing

Other information

- Store between 15-30ºC (59-86°F)
- Avoid freezing and excessive heat above 40ºC(104°F)

Inactive ingredients

Water, glycerin, aloe barbadensis (aloe vera) leaf extract, hydrogen peroxide, tocopheryl acetate (Vitamin E), propylene glycol, peg-60 hydrogenated castor oil, phenoxyethanol

Package Label

Kids Antiseptic 80 wipes, 454g, NDC: 76523-098-090